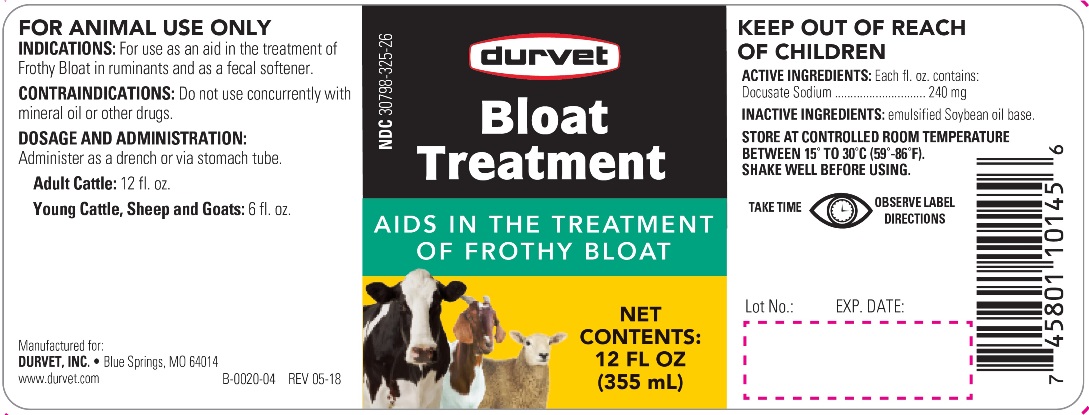 DRUG LABEL: BLOAT TREATMENT
NDC: 30798-325 | Form: EMULSION
Manufacturer: Durvet, Inc.
Category: animal | Type: OTC ANIMAL DRUG LABEL
Date: 20180625

ACTIVE INGREDIENTS: DOCUSATE SODIUM 240 mg/29.57 mL

BLOAT TREATMENT

INDICATIONS AND USAGE

AIDS IN THE TREATMENT OF FROTHY BLOAT

FOR ANIMAL USE ONLY

KEEP OUT OF REACH OF CHILDREN

INDICATIONS

For use as an aid in the treatment of frothy bloat in ruminants and as a fecal softener.

CONTRAINDICATIONS

Do not use concurrently with mineral oil or other drugs.

DOSAGE AND ADMINISTRATION

Administer as a drench or via stomach tube.

Adult Cattle: 12 fl. oz.

Young Cattle, Sheep and Goats: 6 fl. oz.

COMPOSITION

Active Ingredient: Each fl. oz. contains:
Docusate Sodium ................. 240 mg

Inactive Ingredient: emulsified Soybean oil base.

STORAGE AND HANDLING

STORE AT CONTROLLED ROOM TEMPERATURE BETWEEN 15o and 30oC (59o-86oF).
SHAKE WELL BEFORE USING
TAKE TIME OBSERVE LABEL DIRECTIONS